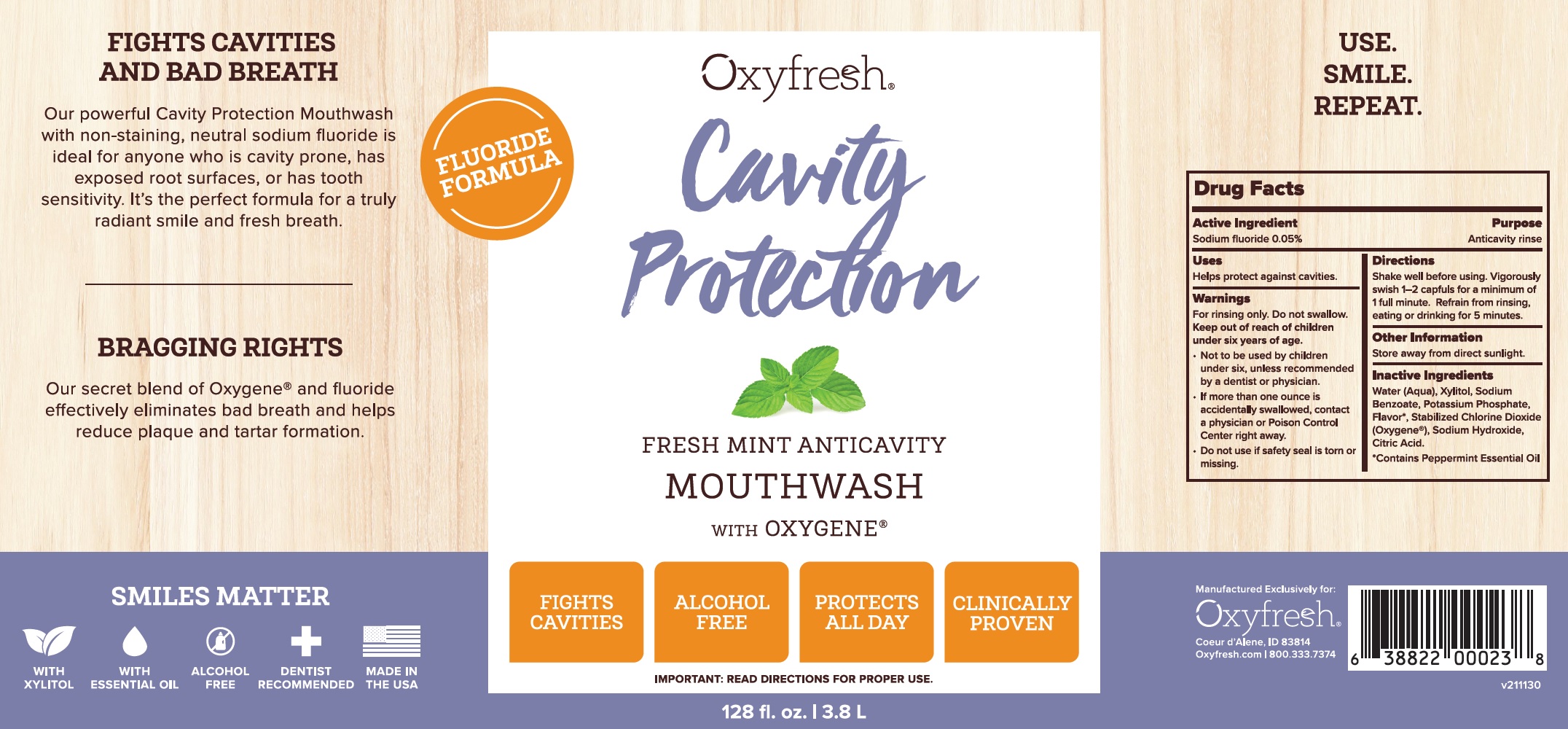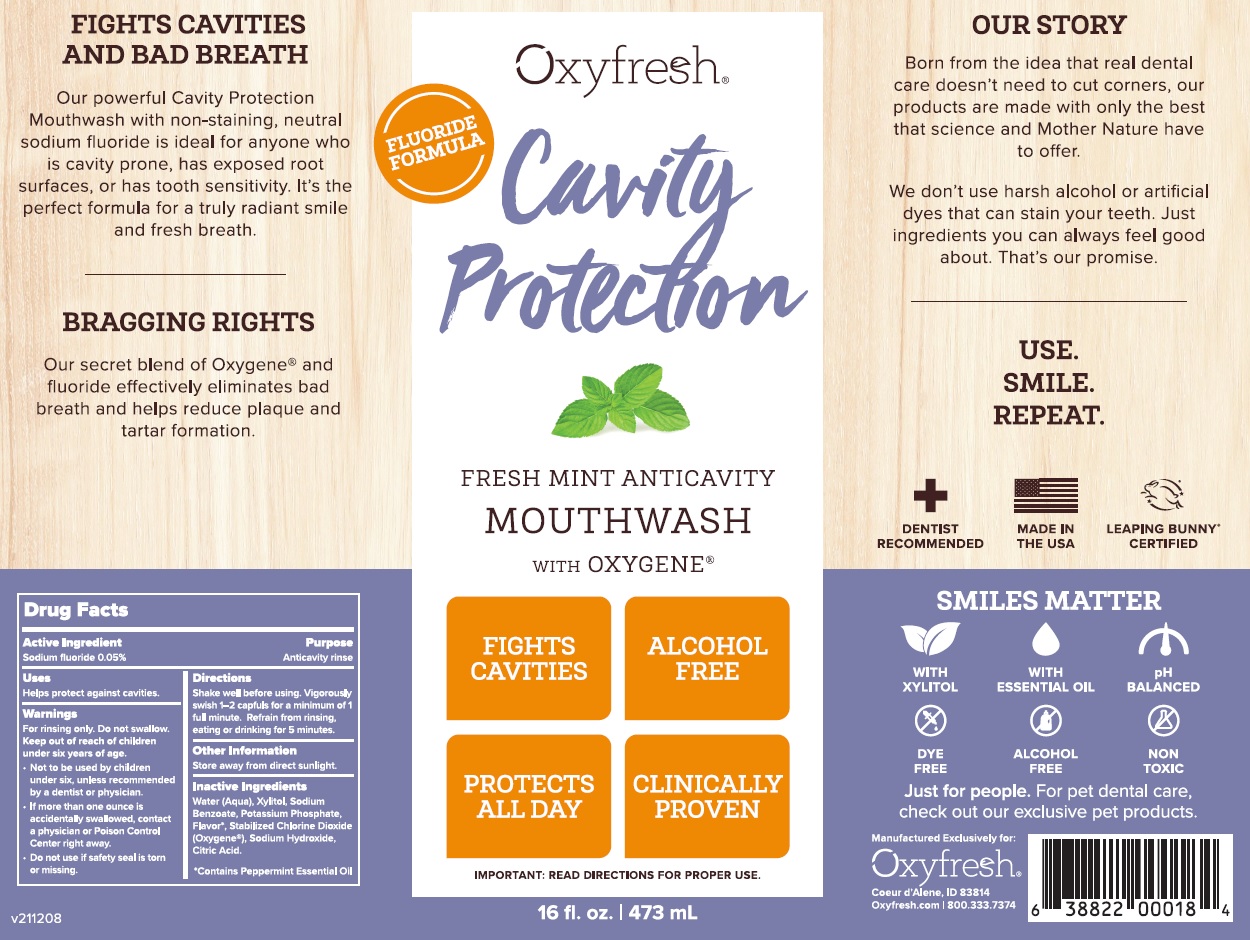 DRUG LABEL: Cavity Protection Fresh Mint Anticavity Mouthwash
NDC: 63615-001 | Form: MOUTHWASH
Manufacturer: Oxyfresh Worldwide Inc
Category: otc | Type: HUMAN OTC DRUG LABEL
Date: 20250910

ACTIVE INGREDIENTS: SODIUM FLUORIDE 0.5 mg/1 mL
INACTIVE INGREDIENTS: CHLORINE DIOXIDE; WATER; XYLITOL; SODIUM BENZOATE; POTASSIUM PHOSPHATE, UNSPECIFIED FORM; OXYGEN; SODIUM HYDROXIDE; CITRIC ACID MONOHYDRATE

Cavity Protection Fresh Mint Anticavity Mouthwash

Active ingredient

Sodium fluoride 0.05%

Purpose

Anticavity rinse

Uses

Helps protect against cavities.

Warnings

For rinsing only. Do not swallow.

Keep out of reach of children

under six years of age.

- Not to be used by children under six, unless recommended by a dentist or physician.
- If more than one ounce is accidentally swallowed, contact a physician or Poison Control Center right away.

Do not use

if safety seal is torn or missing.

Directions

Shake well before using. Vigorously swish 1-2 capfuls for a minimum of 1 full minute. Refrain from rinsing, eating or drinking for 5 minutes.

Other information

Store away from direct sunlight.

INGREDIENTs

Water (Aqua), Xylitol, Sodium Benzoate, Potassium Phosphate, Flavor*, Stabilized Chlorine Dioxide (Oxygene), Sodium Hydroxide, Citric Acid.

*Contains Peppermint Essential Oil